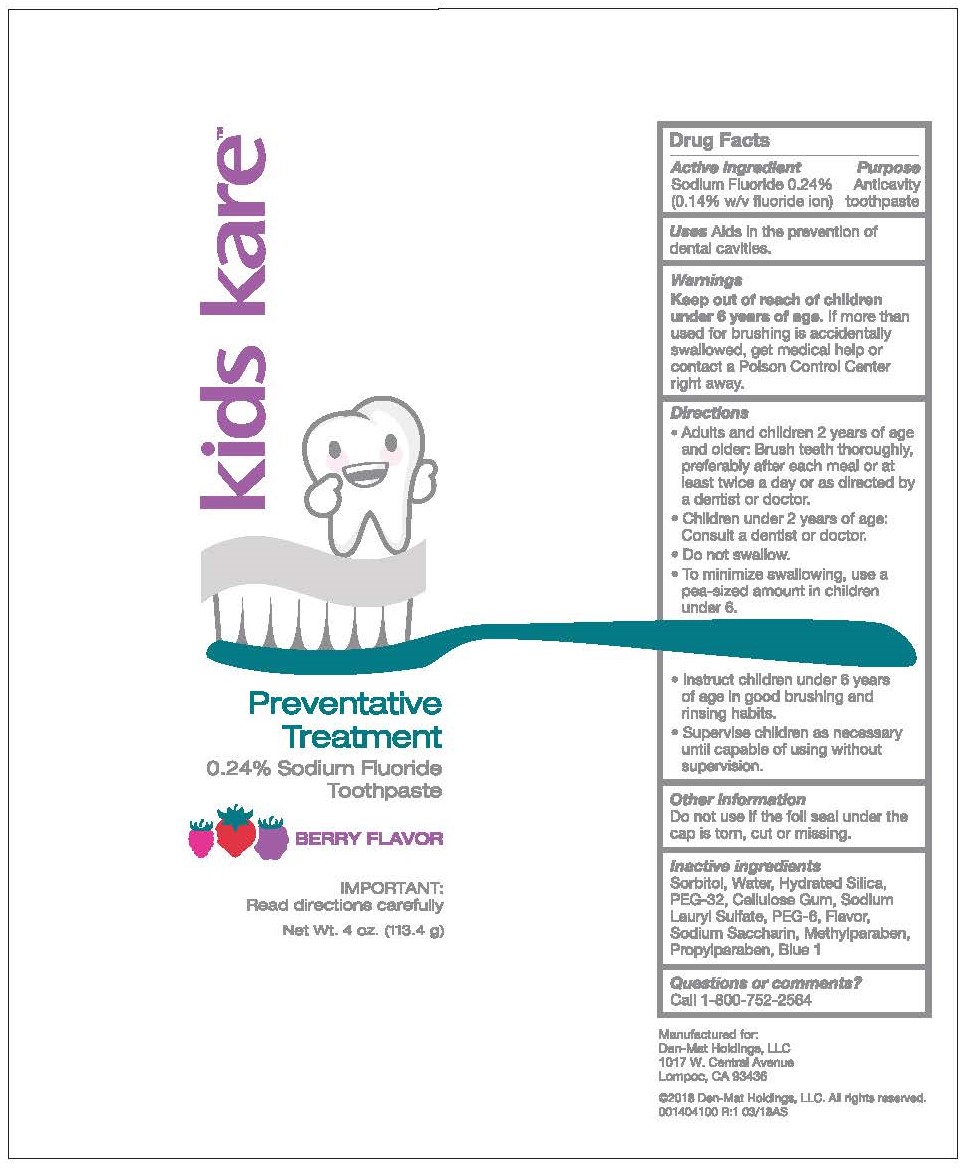 DRUG LABEL: Kids Kare
NDC: 59883-718 | Form: PASTE, DENTIFRICE
Manufacturer: DEN-MAT HOLDINGS, LLC.
Category: otc | Type: HUMAN OTC DRUG LABEL
Date: 20241231

ACTIVE INGREDIENTS: SODIUM FLUORIDE 2.4 mg/1 g
INACTIVE INGREDIENTS: METHYLPARABEN; SORBITOL; PROPYLPARABEN; POLYETHYLENE GLYCOL 1450; HYDRATED SILICA; SODIUM LAURYL SULFATE; CARBOXYMETHYLCELLULOSE; BERRY; POLYETHYLENE GLYCOL 300; WATER; FD&C BLUE NO. 1; SACCHARIN SODIUM

Kids Kare - Toothpaste

Active ingredient

Sodium Fluoride 0.24% (0.14% w/v fluoride ion)

Purpose

Anticavity toothpaste

Uses

Aids in the prevention of dental cavities.

Keep out of reach of children under 6 years of age.If more than used for brushing is accidentally swallowed, get medical help or contact a Poison Control Center right away.

Directions

- Adults and children 2 years of age or older: Brush teeth thoroughly, preferably after each meal or at least twice a day or as directed by a dentist or doctor.
- Children under 2 years of age: Consult a dentist or doctor.
- Do not swallow.
- To minimize swallowing, use a pea-sized amount in children under 6.
- Instruct children under 6 years of age in good brushing and rinsing habits.
- Supervise children as necessary until capable of using without supervision.

Other information

Do not use if the foil seal under the cap is torn, cut or missing.

Inactive ingredients

Sorbitol, Water, Hydrated Silica, PEG-32, Cellulose Gum, Sodium Lauryl Sulfate, PEG-6, Flavor, Sodium Saccharin, Methylparaben, Propylparaben, Blue 1

Questions or comments?

Call 1-800-752-2564

Principal Display Panel

kids kare™

Preventative

Treatment

0.24% Sodium Fluoride

Toothpaste

Berry Flavor

IMPORTANT:

Read directions carefully

Net Wt. 4 oz. (113.4 g)